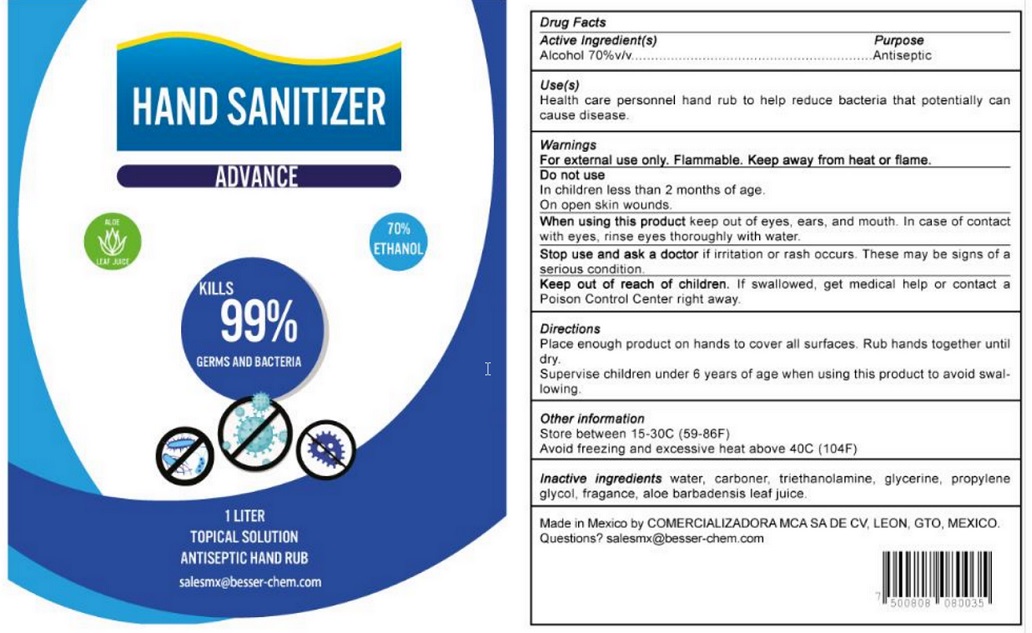 DRUG LABEL: Hand Sanitizer Advance
NDC: 80717-001 | Form: GEL
Manufacturer: Comercializadora Mca, S.A. de C.V.
Category: otc | Type: HUMAN OTC DRUG LABEL
Date: 20201008

ACTIVE INGREDIENTS: ALCOHOL 70 mL/100 mL
INACTIVE INGREDIENTS: WATER; CARBOMER HOMOPOLYMER, UNSPECIFIED TYPE; GLYCERIN; BACKHOUSIA CITRIODORA LEAF OIL; ALOE VERA LEAF; PROPYLENE GLYCOL

Active Ingredient

Alcohol 70% v/v.

Purpose

Antiseptic

Use

Health care personnel hand rub to help reduce bacteria that potentially can cause disease.

Warnings

For external use only. Flammable. Keep away from heat or flame.

Do not use

- in children less than 2 months of age
- on open skin wounds

When using this product keep out of eyes, ears, and mouth. In case of contact with eyes, rinse eyes thoroughly with water.

Stop use and ask a doctor if irritation or rash occurs. These may be signs of a serious condition.

Keep out of reach of children. If swallowed, get medical help or contact a Poison Control Center right away.

Directions

- Place enough product on hands to cover all surfaces. Rub hands together until dry.
- Supervise children under 6 years of age when using this product to avoid swallowing.

Other information

- Store between 15-30C (59-86F)
- Avoid freezing and excessive heat above 40C (104F)

Inactive ingredients

Water, carboner, triethanolamine, glycerine, propylene glycol, fragrance, aloe barbadensis leaf juice.

Made in Mexico by COMERCIALIZADORA MCA SA DE CV, LEON, GTO, MEXICO.
Questions? salesmx@besser-chem.com